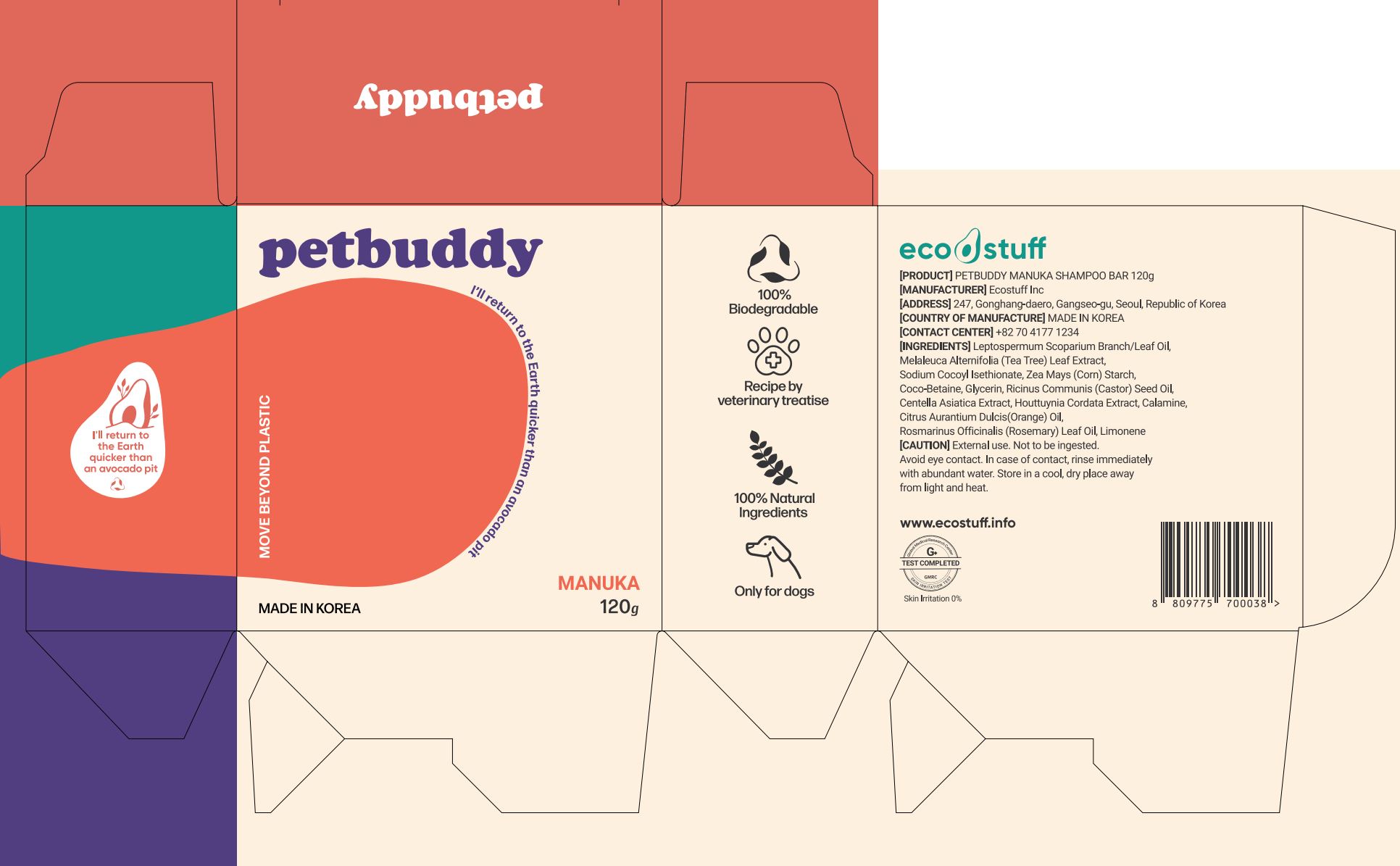 DRUG LABEL: PETBUDDY MANUKA SHAMPOOBAR
NDC: 86165-0001 | Form: SOAP
Manufacturer: Ecostuff Inc.
Category: animal | Type: OTC ANIMAL DRUG LABEL
Date: 20221120

ACTIVE INGREDIENTS: MANUKA OIL 1 g/100 g
INACTIVE INGREDIENTS: SODIUM COCOYL ISETHIONATE; GLYCERIN

ACTIVE INGREDIENT

Leptospermum Scoparium Branch Leaf Oil

INACTIVE INGREDIENT

sodium cocoyl isethionate, zea mays starch, coco betaine, glycerin, etc

PURPOSE

Pet Hygiene Cleanliness

WARNINGS

External use. Not to be ingested. Avoid eye contact. In case of contact, rinse immediately with abundant water. Store in a cool, dry place away from light and heat.

Keep Out of Reach of Children

INDICATIONS AND USAGE

ecostuff bar lathers up really quickly, whether you apply it directly to your wet pet, or if you rub it in your palms or ecostuff organic cotton bag and then into your pet.
Store your bar in a dry place, away from running water.

DOSAGE AND ADMINISTRATION

for external use only